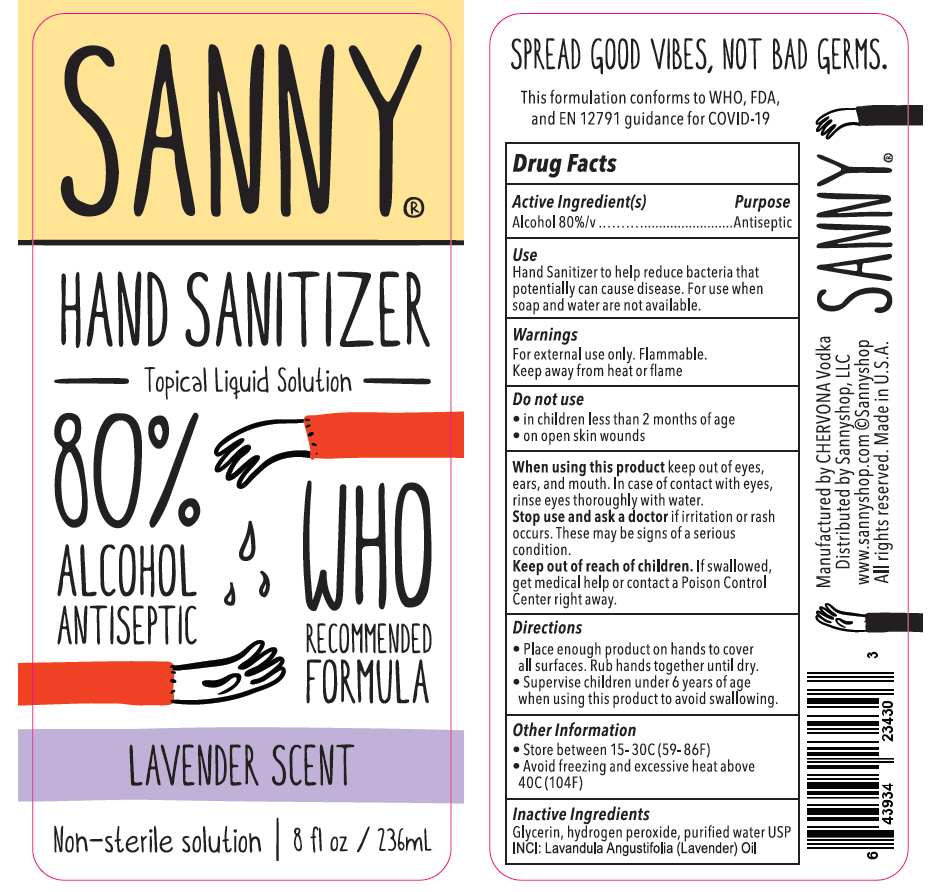 DRUG LABEL: SANNY HAND SANITIZER
NDC: 78930-001 | Form: LIQUID
Manufacturer: Sanny Shop LLC
Category: otc | Type: HUMAN OTC DRUG LABEL
Date: 20201228

ACTIVE INGREDIENTS: Alcohol 80 mL/100 mL
INACTIVE INGREDIENTS: GLYCERIN; HYDROGEN PEROXIDE; WATER; LAVENDER OIL

SANNY® HAND SANITIZER

Drug Facts

Active Ingredient(s)

Alcohol 80%/v

Purpose

Antiseptic

Use

Hand Sanitizer to help reduce bacteria that potentially can cause disease. For use when soap and water are not available.

Warnings

For external use only. Flammable. Keep away from heat or flame

Do Not Use

- in children less than 2 months of age
- on open skin wounds

When using this product keep out of eyes, ears, and mouth. In case of contact with eyes, rinse eyes thoroughly with water. Stop use and ask a doctor if irritation or rash occurs. These may be signs of a serious condition.

Keep out of reach of children. If swallowed, get medical help or contact a Poison Control Center right away.

Directions

- Place enough product on hands to cover all surfaces. Rub hands together until dry.
- Supervise children under 6 years of age when using this product to avoid swallowing.

Other Information

- Store between 15- 30C (59- 86F)
- Avoid freezing and excessive heat above 40C (104F)

Inactive Ingredients

Glycerin, hydrogen peroxide, purified water USP

INCI: Lavandula Angustifolia (Lavender) Oil

Manufactured by CHERVONA Vodka
Distributed by Sannyshop, LLC

PRINCIPAL DISPLAY PANEL - 236 mL Bottle Label

SANNY®

HAND SANITIZER

Topical Liquid Solution

80%
ALCOHOL
ANTISEPTIC

WHO
RECOMMENDED
FORMULA

LAVENDER SCENT

Non–sterile solution | 8 fl oz / 236mL